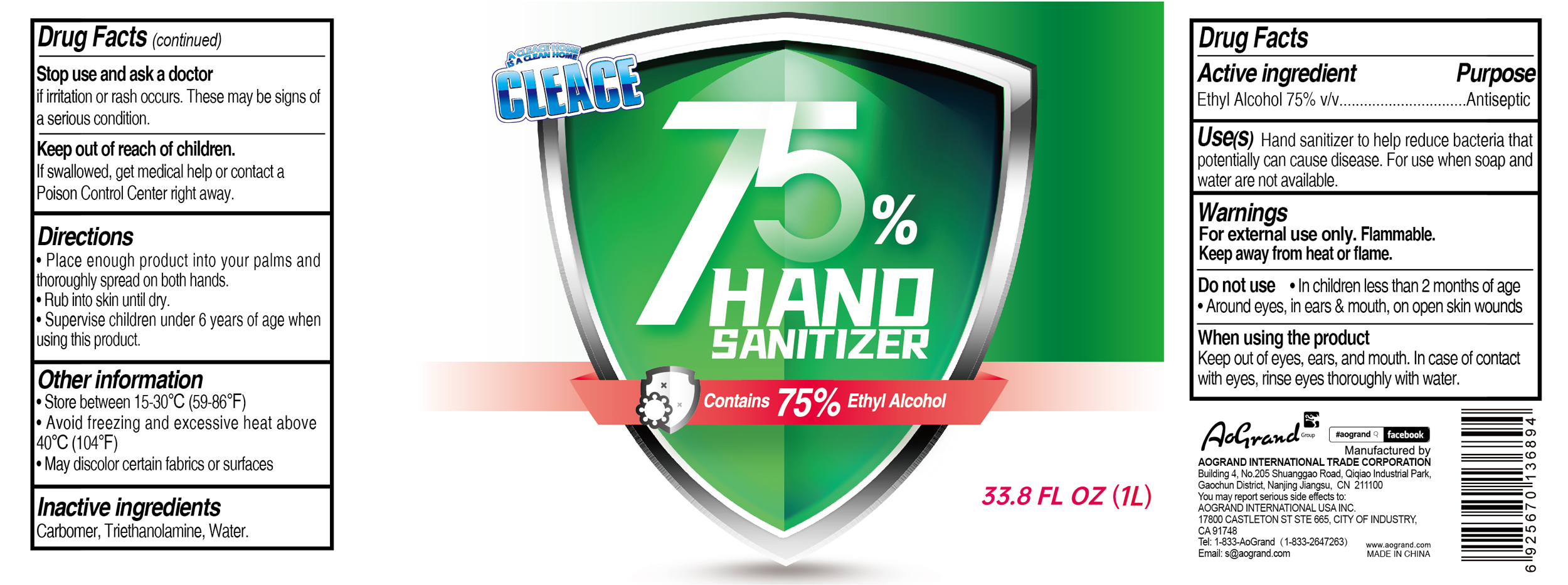 DRUG LABEL: CLEACE 75% Alcohol hand sanitizer
NDC: 74621-014 | Form: GEL
Manufacturer: Aogrand International Trade Corporation
Category: otc | Type: HUMAN OTC DRUG LABEL
Date: 20230211

ACTIVE INGREDIENTS: ALCOHOL 750 mL/1 L
INACTIVE INGREDIENTS: CARBOMER HOMOPOLYMER, UNSPECIFIED TYPE; WATER; TROLAMINE

CLEACE 75% Alcohol hand sanitizer

Active Ingredient

Alcohol 75% v/v. Purpose: Antiseptic

Purpose

Antiseptic, Hand Sanitizer

Uses

Hand sanitizer to help decrease bacteria on the skinthat can cause disease. For use when soap and water are not available.

Warnings

For external use only. Flammable.

Keep away from fire or flame.

Do not use

- in children less than 2 months of age.
- Around eyes, in ears & mouth, on open skin wounds

When using this product

Keep out of eyes, ears, and mouth. In case of contact with eyes, rinse eyes thoroughly with water

Stop use and ask a doctor

if irritation or rash occurs. These may be signs of a serious conditions

Keep out of reach of children.

if swallowed, get medical help or contact a Poison Control Center right away.

Directions

- place enough product into your palms and thoroughly spread on both hands.
- rub into skin until dry.
- Supervise children under 6 years of age when using this product.

Other information

- Store between 15-30C (59-86F)
- Avoid freezing and excessive heat above 40C (104F)
- May discolor certain fabrics or surfaces.

Inactive ingredients

carbomer, triethanolamine, water

Package Label - Principal Display Panel

1L NDC: 74621-014-01

A CLEACE HOME

IS A CLEAN HOME

CLEACE

75% Hand Sanitizer

Contain 75% Ethyl Alcohol

33.8 FL OZ

1L